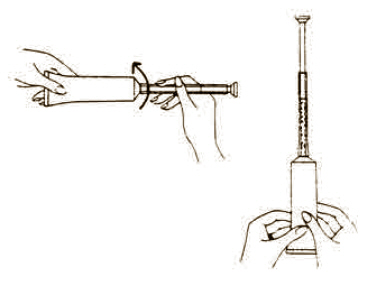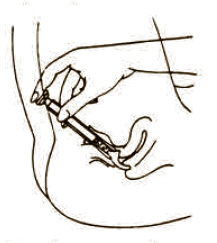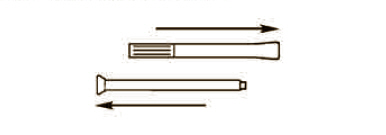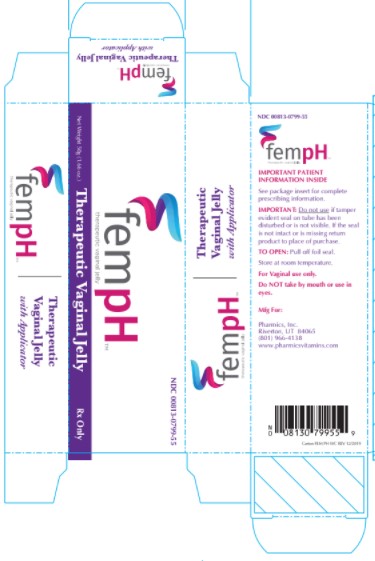 DRUG LABEL: Fem pH
NDC: 0813-0799 | Form: JELLY
Manufacturer: Pharmics, Inc.
Category: prescription | Type: HUMAN PRESCRIPTION DRUG LABEL
Date: 20230118

ACTIVE INGREDIENTS: ACETIC ACID 0.009 g/1 g; OXYQUINOLINE SULFATE 0.00025 g/1 g
INACTIVE INGREDIENTS: GLYCERIN; LACTIC ACID; POLYETHYLENE GLYCOL 4500; WATER; POTASSIUM HYDROXIDE

Fem pH™
Therapeutic Vaginal Jelly

Rx Only

Description

Fem pH Vaginal Jelly is a bland, non-irritating water dispersible, buffered acid jelly for intravaginal use. Fem pH is classified as a Vaginal Therapeutic Jelly. Fem pH contains 0.9% glacial acetic acid (C2H402) and 0.025% oxyquinoline sulfate (C18H16N206S) compounded with glycerin, lactic acid, poly ethylene glycol 4500 and purified water. Fem pH is formulated to pH 3.8-4.3 and is adjusted using 1 N potassium hydroxide.

Clinical Pharmacology

Fem pH acts to restore and maintain normal vaginal acidity through its buffered action.

Indications and Usage

Fem pH is indicated as adjunctive therapy in those cases where restoration and maintenance of vaginal acidity is desirable.

Contraindications

None known.

Warnings

No serious adverse reactions or potential safety hazard have been reported with the use of Fem pH.

Precautions

General

No special care is required for the safe and effective use of Fem pH.

Drug Interactions

No incidence of drug interactions has been reported with concomitant use of Fem pH and any other medication.

Laboratory Tests

The monitoring of vaginal acidity (pH) may be helpful in following the patient's response. (The normal vaginal pH has been shown to be in the range of 4.0 to 5.0)

Carcinogenesis

No long-term studies in animals have been performed to evaluate carcinogenic potential.

Pregnancy

Pregnancy Category C

Animal reproduction studies have not been conducted with Fem pH. It is not known whether Fem pH can cause fetal harm when administered to a pregnant woman or can affect reproduction capacity. Fem pH should be given to a pregnant woman only if clearly needed.

Nursing Mothers

It is not known whether this drug is excreted in human milk. Because many drugs are excreted in human milk, caution should be exercised when Fem pH is administered to a nursing woman.

Adverse Reactions

Occasional cases of local stinging and burning have been reported.

Dosage and Administration

The usual dose is one applicator full, administered intra-vaginally, morning and evening. Duration of treatment may be determined by the patient's response to therapy. Each tube has a tamper evident seal at the opening of the tube. Replace cap after each use. To fill applicator screw applicator clockwise onto the tube. Squeeze tube forcing Fem pH jelly into barrel until it is full. Then unscrew applicator counter-clockwise to remove from tube. Lie on your back with knees drawn up. Hold filled applicator by the barrel and gently insert it into the vagina as far as it will comfortably go. Press plunger to empty the contents. Keep the plunger depressed and remove the applicator from vagina. After each use pull applicator apart and wash with warm soapy water, rinse well, dry and reassemble.

How Supplied

50g Tube (NDC 00813-0799-55) with Fem pH applicator.

STORAGE AND HANDLING

Keep this and all medication out of the reach of children. In case of accidental overdose, call a doctor or poison control center immediately.

Store at controlled room temperature 59°-86°F (15°-30°C)

Therapeutic Vaginal Jelly

Directions for using Fem pH applicator.

Each tube has a tamper evident seal at the opening of the tube. Replace cap after each use.

To fill applicator screw applicator clockwise onto the tube. Squeeze tube forcing Fem pH jelly into barrel until it is full. Then unscrew applicator counter-clockwise to remove from tube.

Lie on your back with knees drawn up. Hold filled applicator by the barrel and gently insert it into the vagina as far as it will comfortably go. Press plunger to empty the contents. Keep the plunger depressed and remove the applicator from vagina.

After each use pull applicator apart and wash with warm soapy water, rinse well, dry and reassemble.

PRINCIPAL DISPLAY PANEL - 50g Tube Box

NDC 00813-0799-55

Rx Only

Fem pH™
Therapeutic Vaginal Jelly

Net Weight 50g
(1.66 oz.)

pharmicsINC